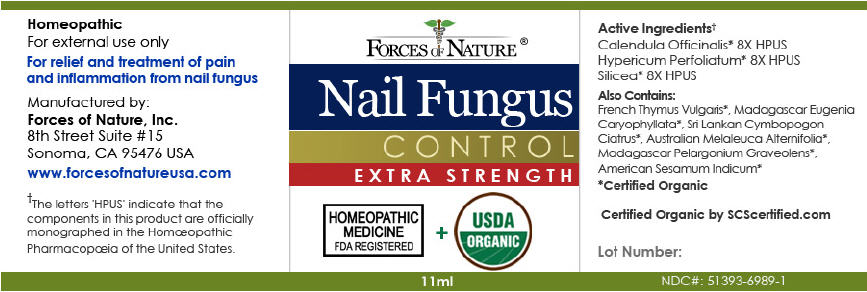 DRUG LABEL: Nail Fungus Control 
NDC: 51393-6989 | Form: SOLUTION/ DROPS
Manufacturer:  Forces of Nature
Category: homeopathic | Type: HUMAN OTC DRUG LABEL
Date: 20210519

ACTIVE INGREDIENTS: Calendula Officinalis Flowering Top 8 [hp_X]/1000 mL; Silicon Dioxide 8 [hp_X]/1000 mL; HYPERICUM PERFORATUM WHOLE 8 [hp_X]/1000 mL
INACTIVE INGREDIENTS: Tea Tree Oil; Geranium Oil, Algerian Type; Clove Oil; East Indian Lemongrass Oil; Thyme Oil; Sesame Oil

Nail Fungus Control
Extra Strength

Drug Facts

ACTIVE INGREDIENT

PURPOSE

Active Ingredients [The letters 'HPUS' indicate that the component(s) in this product is (are) officially monographed in the Homœopathic Pharmacopœia of the United States.] Equal parts of: | Purpose
Calendula Officinalis 8X HPUS | Promotes healthy skin and healing
Hypericum perfoliatum 8X HPUS | Remedy for difficulties with nails
Silicea 8X HPUS | Remedy for nail ulcers, fowl smelling, crippled nails

Also Includes

Certified Organic oils of: East Indian Lemongrass, Pelargonium Graveolens Leaf, Sesame Seed, Tea Tree, French Thyme, South East Asian Clove

Directions

Wash and thoroughly dry the affected area. Apply 1-2 drops and gently rub into affected area 3 times per day. Wash hands afterwards.

Indications

For the relief and treatment of pain, soreness and inflammation from nail fungus.

Warnings

ASK DOCTOR

If skin symptoms worsen, redness, bleeding or pus occurs consult a health care professional.

KEEP OUT OF REACH OF CHILDREN

Keep out of the reach of children. If accidental ingestion of several drops, get medical help or contact a Poison Control Center.

DO NOT USE

For external use only, do not apply to the eyes or mucous membranes.

KEEP OUT OF REACH OF CHILDREN

Keep all medicines out of the reach of children.

PRINCIPAL DISPLAY PANEL - 11ml Bottle Label

FORCES OF NATURE ®

Nail Fungus
CONTROL
EXTRA STRENGTH

HOMEOPATHIC
MEDICINE
FDA REGISTERED
+
USDA
ORGANIC

11ml